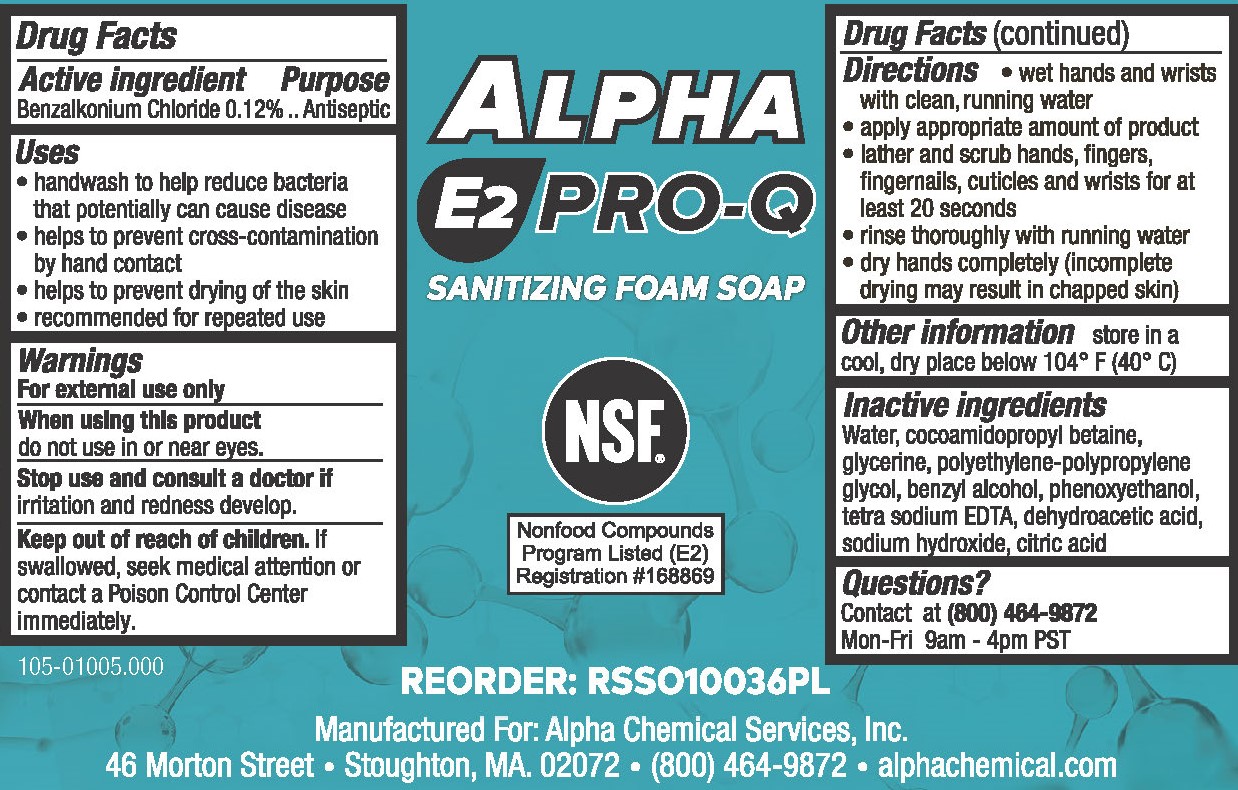 DRUG LABEL: Alpha E2 Pro-Q Sanitizing Foam
NDC: 69335-004 | Form: SOAP
Manufacturer: Alpha Chemical Services, Inc.
Category: otc | Type: HUMAN OTC DRUG LABEL
Date: 20250729

ACTIVE INGREDIENTS: BENZALKONIUM CHLORIDE 1.2 g/1000 mL
INACTIVE INGREDIENTS: EDETATE SODIUM; CITRIC ACID MONOHYDRATE; SODIUM HYDROXIDE; GLYCERIN; POLOXAMER 124; DEHYDROACETIC ACID; WATER; COCAMIDOPROPYL BETAINE; BENZYL ALCOHOL; PHENOXYETHANOL

ALPHA E2 PRO-Q Sanitizing Foam Soap 69335-004

Active ingredient

Benzalkonium Chloride 0.12%

Purpose

Antiseptic

Uses

- handwash to help reduce bacteria that potentially can cause disease
- helps to prevent cross-contamination by hand contact
- helps to prevent drying of the skin
- recommended for repeated use

Warnings

For external use only

When using this product do not use in or near eyes.

Stop use and consult a doctor if irritation and redness develop.

Keep out of reach of children.

If swallowed, seek medical attention or contact a Poison Control Center immediately.

Directions

- wet hands and wrists with clean, running water
- apply appropriate amount of product
- lather and scrub hands, fingers, fingernails, cuticles and wrists for at least 20 seconds
- rinse thoroughly with running water
- dry hands completely (incomplete drying may result in chapped skin)

Other information

store in a cool, dry place below 104° F (40° C)

Inactive ingredients

Water, cocamidopropyl betaine, glycerin, polethylene-polypropylene glycol, benzyl alcohol, phenoxyethanol, tetra sodium EDTA, dehydroacetic acid, sodium hydroxide, citric acid

Questions?

Contact at (800) 464-9872

Mon-Fri 9am - 4pm EDT

PACKAGE LABEL

ALPHA

E2 PRO-Q

SANITIZING FOAM SOAP

NSF

Nonfood Compounds

Program Listed (E2)

Registration #168869

REORDER: RSSO10036PL

Manufactured For: Alpha Chemical Services, Inc.

46 Morton Street • Stoughton, MA. 02072 • (800) 464-9872 • alphachemical.com